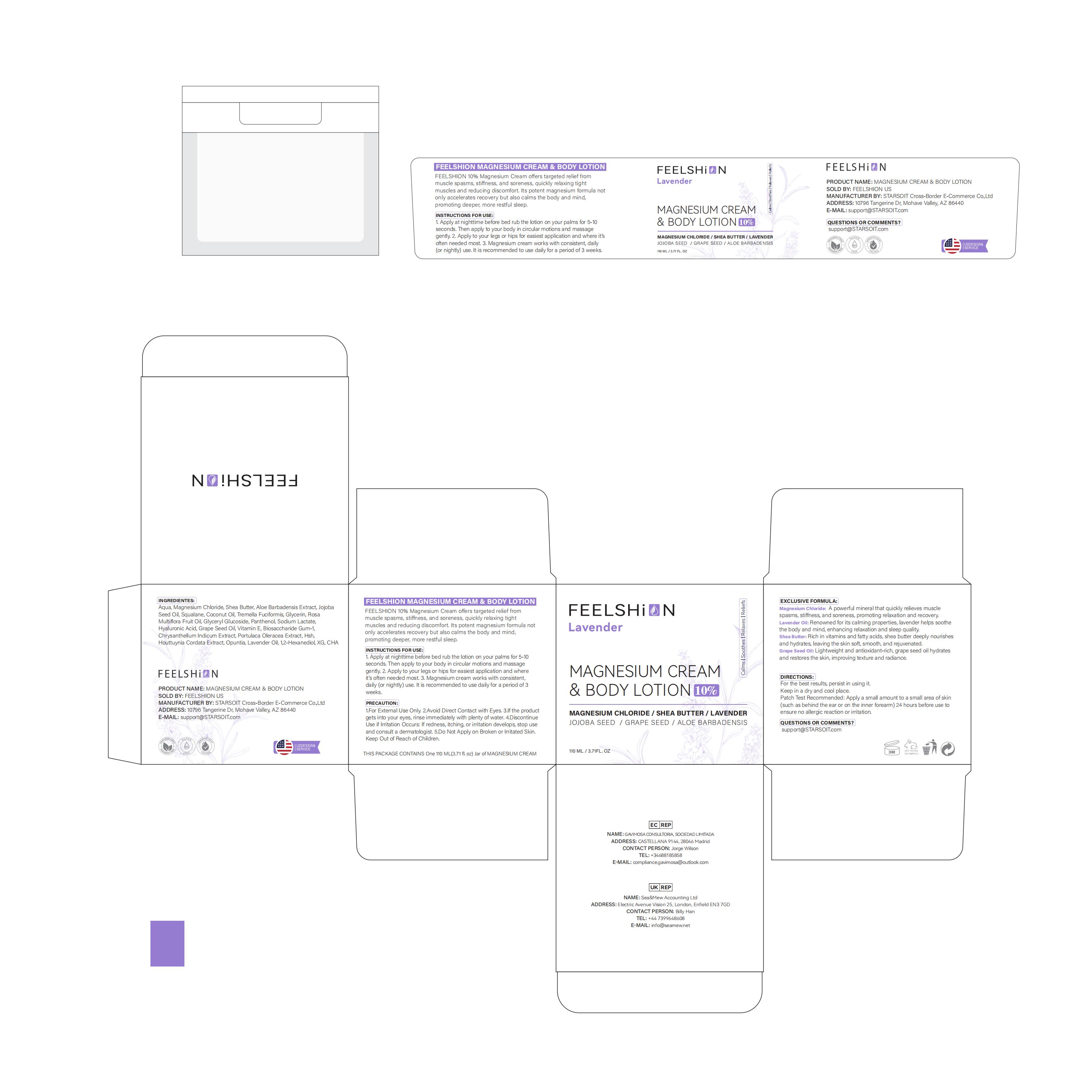 DRUG LABEL: FEELSHION Lavender Magnesium
NDC: 85212-0037 | Form: CREAM
Manufacturer: Beijing JUNGE Technology Co., Ltd.
Category: otc | Type: HUMAN OTC DRUG LABEL
Date: 20250514

ACTIVE INGREDIENTS: SHEA BUTTER 3 g/100 mL
INACTIVE INGREDIENTS: VITIS VINIFERA (GRAPE) SEED OIL 0.5 mL/100 mL; SIMMONDSIA CHINENSIS (JOJOBA) SEED OIL 2 mL/100 mL; ROSA MULTIFLORA FRUIT 1 mL/100 mL; TOCOPHEROL 0.5 mL/100 mL; BIOSACCHARIDE GUM-1 0.2 mL/100 mL; TREMELLA FUCIFORMIS WHOLE 1 mL/100 mL; PANTHENOL 1 mL/100 mL; PORTULACA OLERACEA WHOLE 0.2 mL/100 mL; ALOE BARBADENSIS LEAF 3 mL/100 mL; SODIUM LACTATE 1 mL/100 mL; COCOS NUCIFERA (COCONUT) OIL 2 mL/100 mL; GLYCERIN 1 mL/100 mL; HOUTTUYNIA CORDATA WHOLE 0.1 mL/100 mL; 1,2-HEXANEDIOL 0.1 mL/100 mL; HYALURONIC ACID 1 mL/100 mL; WATER 70.5 mL/100 mL; SQUALANE 2 mL/100 mL; CHRYSANTHELLUM INDICUM WHOLE 0.2 mL/100 mL; OPUNTIA TUNA FRUIT 0.1 mL/100 mL; LAVANDULA ANGUSTIFOLIA (LAVENDER) OIL 0.1 mL/100 mL; MAGNESIUM CHLORIDE 10 mL/100 mL

WARNINGS

For external use only.

STOP USE

rash occurs.

DO NOT USE

on damaged or broken skin.

WHEN USING

keep out of eyes. Rinse with water to remove.

KEEP OUT OF REACH OF CHILDREN

If swallowed, get medical help or contact a Poison Control Center right away.

PURPOSE

*Helps solve sleep problems
*Promote deep relaxation
*Relieve muscle tension*lmprove sleep quality

WHEN USING

Please use this product before going to bed, apply thisproduct to the neck, shoulders, legs, etc, Gentlymassage for 5-10 seconds until completely absorbed.

ACTIVE INGREDIENT

MAGNESIUM CHLORIDE,SIMMONDSIA CHINENSIS (JOJOBA) SEED OIL,HYALURONIC ACID,VITIS VINIFERA (GRAPE) SEED OIL,TOCOPHEROL,LAVANDULA ANGUSTIFOLIA (LAVENDER) OIL

DOSAGE AND ADMINISTRATION

Apply an appropriate amount of magnesium cream to the desired location.

INACTIVE INGREDIENT

AQUA
BUTYROSPERMUM PARKII (SHEA BUTTER)
ALOE BARBADENSIS FLOWER EXTRACT
SQUALANE
COCOS NUCIFERA (COCONUT) OIL
TREMELLA FUCIFORMIS POLYSACCHARIDE
GLYCERIN
ROSA MULTIFLORA FRUIT EXTRACT
PANTHENOL
SODIUM LACTATE
BIOSACCHARIDE GUM-1
CHRYSANTHELLUM INDICUM EXTRACT
PORTULACA OLERACEA EXTRACT
HOUTTUYNIA CORDATA EXTRACT
OPUNTIA TUNA FRUIT EXTRACT
1,2-HEXANEDIOL

INDICATIONS AND USAGE

Skin